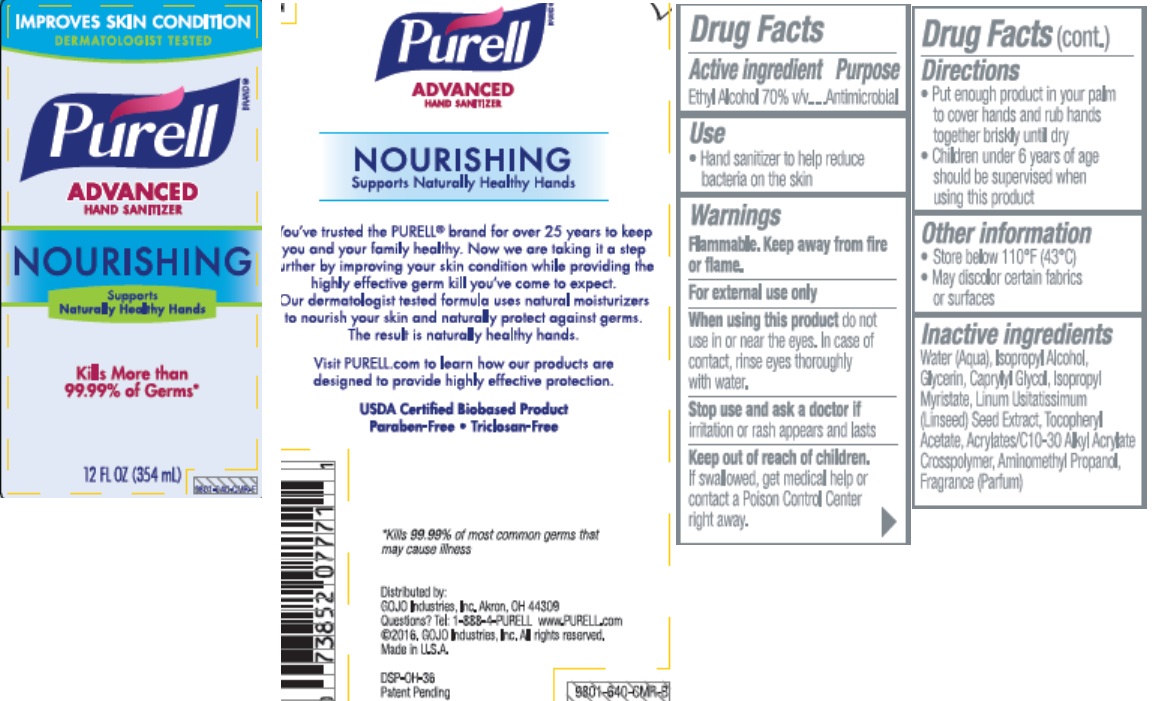 DRUG LABEL: PURELL Advanced Hand Sanitizer Nourishing
NDC: 21749-485 | Form: GEL
Manufacturer: GOJO Industries, Inc.
Category: otc | Type: HUMAN OTC DRUG LABEL
Date: 20180110

ACTIVE INGREDIENTS: ALCOHOL 0.7 mL/1 mL
INACTIVE INGREDIENTS: WATER; ISOPROPYL ALCOHOL; GLYCERIN; CAPRYLYL GLYCOL; ISOPROPYL MYRISTATE; .ALPHA.-TOCOPHEROL ACETATE; CARBOMER INTERPOLYMER TYPE A (ALLYL SUCROSE CROSSLINKED); AMINOMETHYLPROPANOL

PURELL Advanced Hand Sanitizer Nourishing

Active ingredient

Ethyl Alcohol 70%

Purpose

Antimicrobial

Use

Hand sanitizer to help decrease bacteria on skin

Warnings

Flammable. Keep away from fire or flame.

For external use only.

When using this product do not use in or near the eyes. In case of contact, rinse eyes thoroughly with water.

Stop use and ask a doctor if irritation or rash appears and lasts

Keep out of reach of children. If swallowed, get medical help or contact a Poison Control Center right away.

Directions

· Put enough product in your palm to thoroughly cover your hands · Rub hands together briskly until dry · Children under 6 years of age should be supervised when using this product

Other Information

• Store below 110°F (43°C) • May discolor certain fabrics or surfaces

Inactive Ingredients

Water (Aqua), Isopropyl Alcohol, Glycerin, Caprylyl Glycol, Isopropyl Myristate, Linum Usitatissimum (Linseed) Seed Extract, Tocopheryl Acetate, Acrylates/C10-30 Alkyl Acrylate Crosspolymer, Aminomethyl Propanol, Fragrance (Parfum)